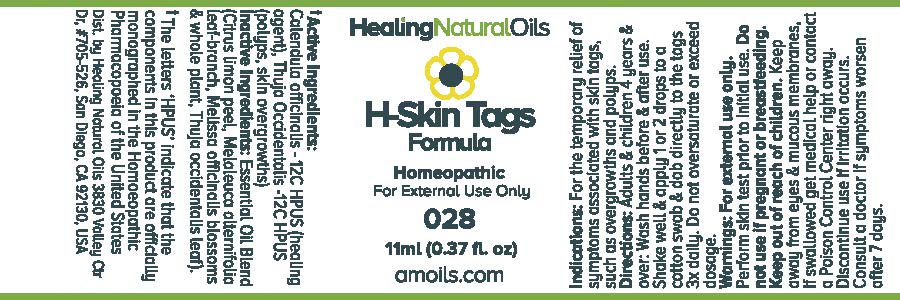 DRUG LABEL: H-Skin Tags Formula
                
NDC: 61077-028 | Form: OIL
Manufacturer: Healing Natural Oils LLC
Category: homeopathic | Type: HUMAN OTC DRUG LABEL
Date: 20171227

ACTIVE INGREDIENTS: CALENDULA OFFICINALIS FLOWERING TOP 12 [hp_C]/11 mL; THUJA OCCIDENTALIS LEAFY TWIG 12 [hp_C]/11 mL
INACTIVE INGREDIENTS: LEMON PEEL; MELALEUCA ALTERNIFOLIA LEAF; MELISSA OFFICINALIS; THUJA OCCIDENTALIS LEAF

Active Ingredients:

Calendula officinalis - 12C HPUS

Thuja occidentalis - 12C HPUS

Purpose

Calendula officinalis -12C HPUS (healing agent),

Thuja occidentalis -12CHPUS (polyps, skin overgrowths)

The letters ‘HPUS’ indicate that the components in this product are officially
monographed in the Homoeopathic Pharmacopoeia of the United States

Inactive Ingredients:

Essential Oil Blend (Citrus limon peel, Melaleuca alternifolia leaf-branch, Melissa officinalis blossoms and
whole plant, Thuja occidentalis leaf)

Indications:

For the temporary relief of symptoms associated with skin tags, such as overgrowths and polyps.

Directions:

Adults and children 4 years and over: Wash hands before and after use.
Shake well and apply 1 or 2 drops to a cotton swab and dab directly to the tags 3x daily.
Do not oversaturate or exceed dosage.

Warnings:

For external use only.
Perform skin test prior to initial use.

Do not use if pregnant or breastfeeding.

Keep out of reach of children.

OTHER SAFETY INFORMATION

Keep away from eyes and mucous membranes. If swallowed get medical help or contact a Poison Control
Center right away.

Discontinue use if irritation occurs.

ASK DOCTOR

Consult a doctor if symptoms worsen after 7 days.

DESCRIPTION

Dist. by Healing Natural Oils 3830 Valley Ctr Dr, #705-526, San Diego, CA 92130, USA

PACKAGE LABEL

Healing Natural Oils

H-Skin Tags

Formula

Homeopathic

For External Use Only

028

11ml (0.37 fl. oz)
amoils.com